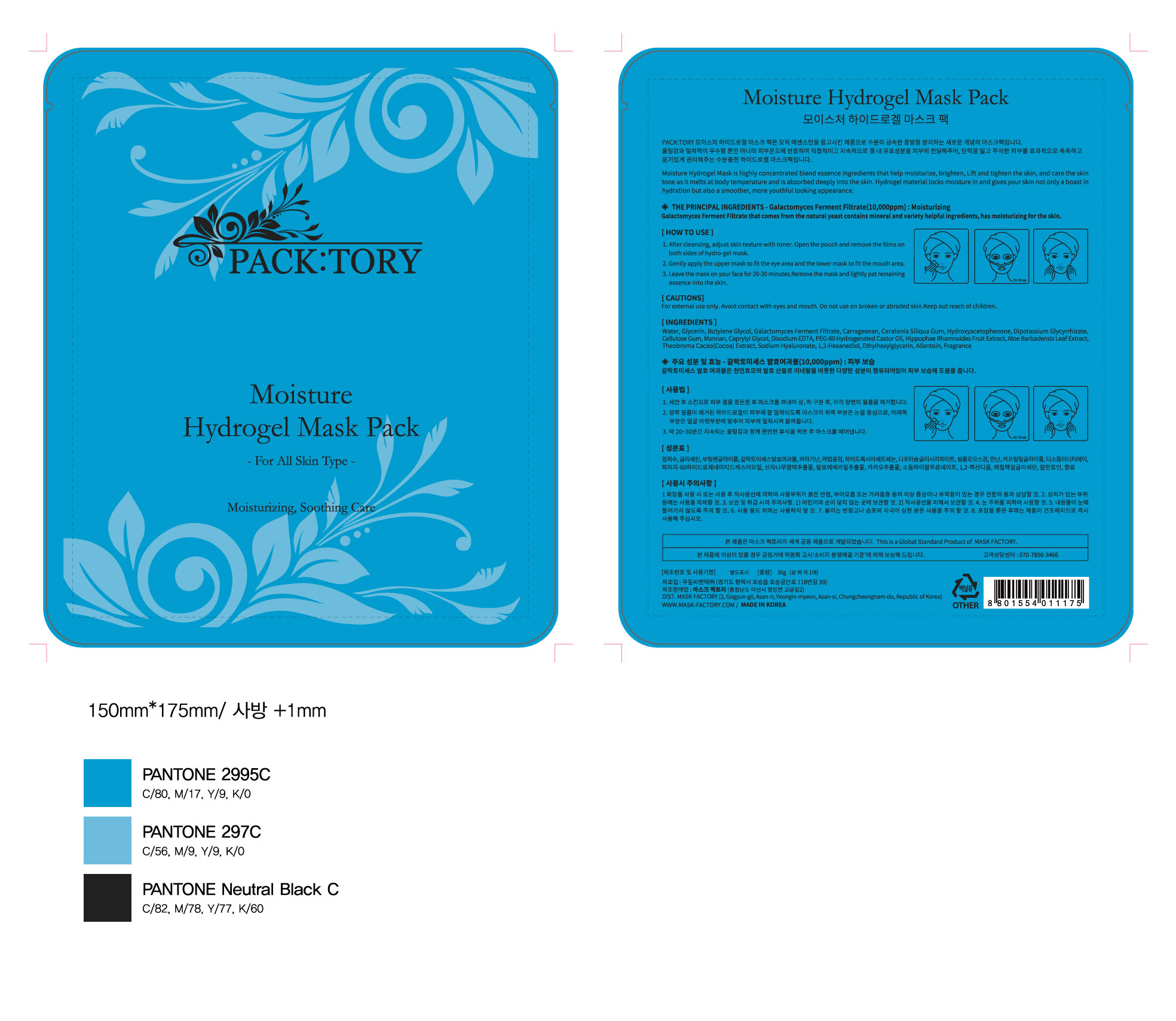 DRUG LABEL: Moisture hydrogel mask pack
NDC: 71820-0002 | Form: LIQUID
Manufacturer: Mask Factory
Category: otc | Type: HUMAN OTC DRUG LABEL
Date: 20171023

ACTIVE INGREDIENTS: GLYCERIN 25 g/100 g
INACTIVE INGREDIENTS: WATER; BUTYLENE GLYCOL

Drug Facts

ACTIVE INGREDIENT

glycerin

INACTIVE INGREDIENT

water, butylene glycol, etc

PURPOSE

anti aging

skin protectant

keep out of reach of the children

INDICATIONS AND USAGE

gently apply the mask to fit your face

leave the mask on yor face for 20~30 minutes

remove the mask and lightly pat remaining

WARNINGS

Cautions :

1. When you use this product and find any of following problems, stop using it. if you keep using it despite the problem, the symptom will get worse, so you will have to go see a dermatologist.

- During use, if you have red spots, swelling, itching, or any other stimuli.

- if the applied region has any problem above for direct light.

2. Do not use the product on wound or dermatitis. 3.Attentive points for storage and treatment :

- Store it in the place where infants or children cannot touch

- do not store it where it has either high or low temperature or there is direct light.

DOSAGE AND ADMINISTRATION

for external use only